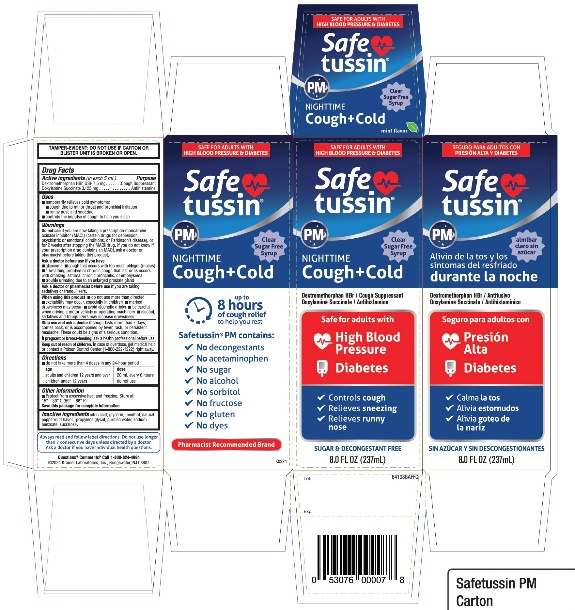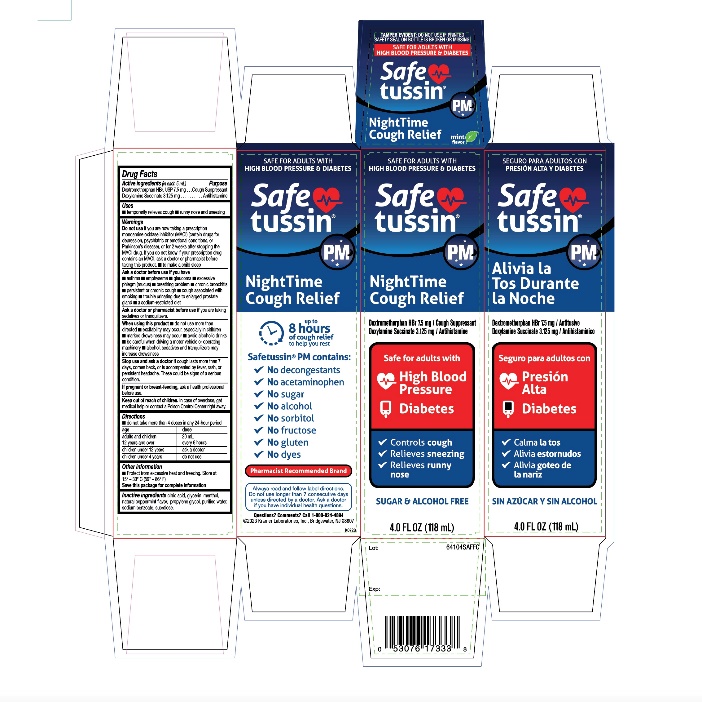 DRUG LABEL: Safetussin PM Nighttime
NDC: 55505-221 | Form: LIQUID
Manufacturer: Kramer Laboratories
Category: otc | Type: HUMAN OTC DRUG LABEL
Date: 20251229

ACTIVE INGREDIENTS: DEXTROMETHORPHAN 7.5 mg/5 mL; DOXYLAMINE SUCCINATE 3.125 mg/5 mL
INACTIVE INGREDIENTS: CITRIC ACID MONOHYDRATE; GLYCERIN; MENTHOL, UNSPECIFIED FORM; MINT; PROPYLENE GLYCOL; WATER; SODIUM BENZOATE; SUCRALOSE

Safetussin PM NightTime Cough Relief Drug Facts

ACTIVE INGREDIENT

Active ingredients (in each 5mL) | Purpose
Dextromethorphan HBr, USP 7.5 mg | Cough Suppressant
Doxylamine Succinate 3.125 mg | Antihistamine

Uses

- temporarily relieves cough
- runny nose and sneezing

Warnings

- Do not useif you are now taking a prescription monoamine oxidase inhibitor (MAOI) (certain drugs for depression, psychiatric or emotional conditions, or Parkinson’s disease), or for 2 weeks after stopping the MAOI drug. If you do not know if your prescription drug contains an MAOI, ask a doctor or pharmacist before taking this product

- .to make a child sleep.

Ask a doctor before use if you have

- asthma
- emphysema
- glaucoma
- excessive phlegm (mucus)
- breathing problem
- chronic bronchitis
- persistent or chronic cough
- cough associated with smoking
- trouble urinating due to enlarged prostate gland
- a sodium-restricted diet

Ask a doctor or pharmacist before use ifyou are taking sedatives or tranquilizers.

When using this product

- do not use more than directed
- excitability may occur, especially in children
- marked drowsiness may occur
- avoid alcoholic drinks
- be careful when driving a motor vehicle or operating machinery
- alcohol, sedatives and tranquilizers may increase drowsiness

Stop use and ask a doctor ifcough lasts more than 7 days, comes back, or is accompanied by fever, rash, or persistent headache. These could be signs of a serious condition.

PREGNANCY OR BREAST FEEDING

If pregnant or breast-feeding,ask a health professional before use.

Keep out of reach of children.In case of overdose, get medical help or contact a Poison Control Center right away.

Directions

- do not take more than 4 doses in any 24-hour period

age | dose
adults and children 12 years and over | 20 mL every 6 hours
children under 12 years | ask a doctor
children under 4 years | do not use

Other information:

- Protect from excessive heat and freezing. Store at 15° - 30° C (59° - 86° F) Save this package for complete information

Inactive ingredients:

citric acid, glycerin, menthol, natural peppermint flavor, propylene glycol, purified water, sodium benzoate, sucralose

PRINCIPAL DISPLAY PANEL

SAFE FOR ADULTS WITH

HIGH BLOOD PRESSURE & DIABETES

Safetussin ®PM
NightTime
Cough Relief
Dextromethorphan HBr 7.5 mg / Cough Suppressant

Doxylamine Succinate 3.125 mg / Antihistamine

Safe for adults with
High Blood Pressure
Diabetes
√ Controls Cough
√ Relieves Sneezing
√ Relieves runny nose
SUGAR & ALCOHOL FREE
4.0 FL OZ (118mL)

SEGURO PARA ADULTOS CON PRESION ALTA Y DIABETES
Safetussin ®PM
Alivia la Tos
Durante la Noche

Dextromethorphan HBr 7.5 mg / Antiusivo

Doxylamine Succinate 3.125 mg / Antihistaminíco
Seguro para adultos con
Presión Alta
Diabetes
√ Calma la tos,
√ Alivia estornudos
√ Alivia goteo de la nariz
SINAZÚCAR Y SINALCOHOL
4 FL. OZ (118 mL)
Safetussin ®PM
NIGHT TIME
COUGH RELIEF
Cough Suppressant / Antihistamine
Up To
8 Hours of cough relief
to help you rest

Safetussin ®PM contains:

√ No decongestants

√ No acetaminophen

√ No sugar

√ No alcohol

√ No sorbitol

√ No fructose

√ No gluten

√ No dyes
Pharmacist Recommended Brand
Always read and follow label directions. Do not use longer than 7 consecutive days unless directed by a doctor. Ask a doctor if you have individual health questions.
Questions? Comments?
Call 1-800-824-4894
© 2023 Kramer Laboratories, Inc.
Bridgewater, NJ 08807 ● kramerlabs.com
K0723

PACKAGE LABEL FOR 4 FL OZ (118 mL)